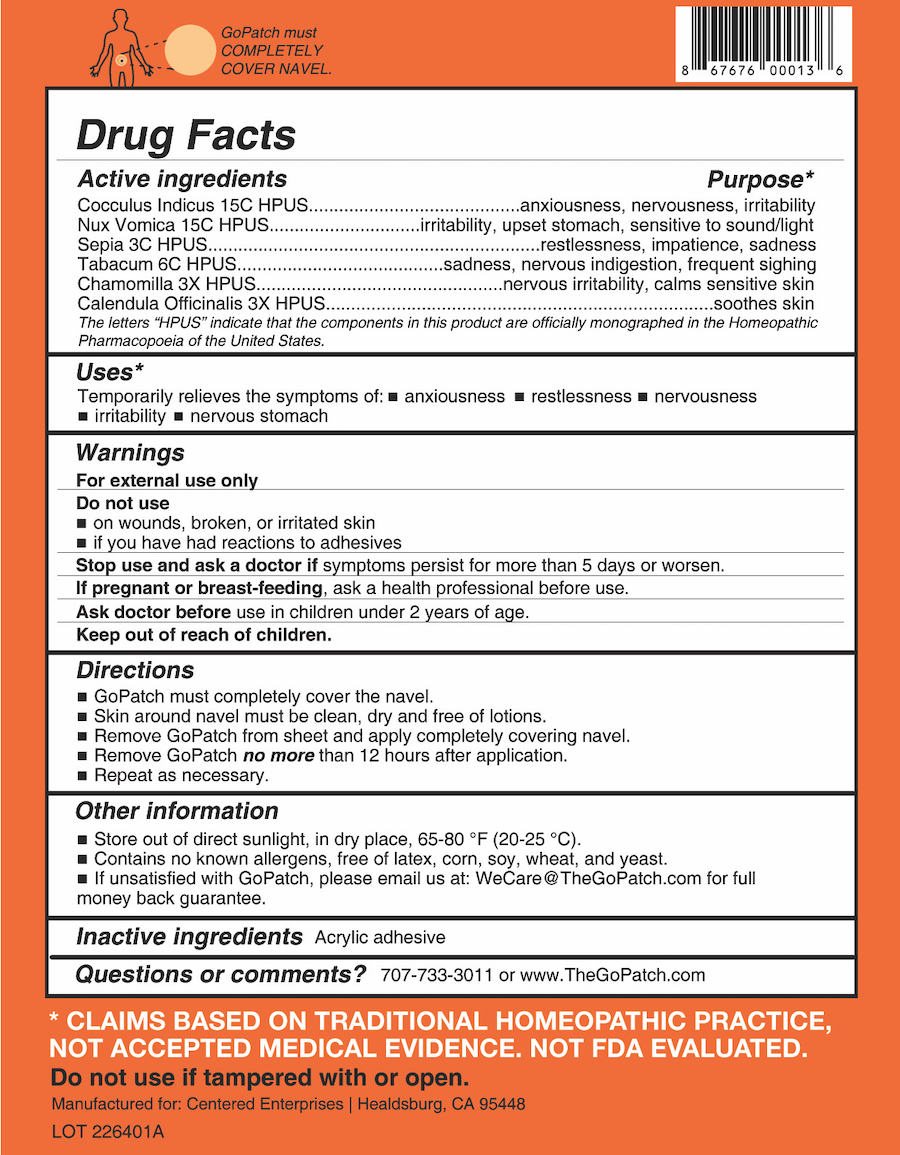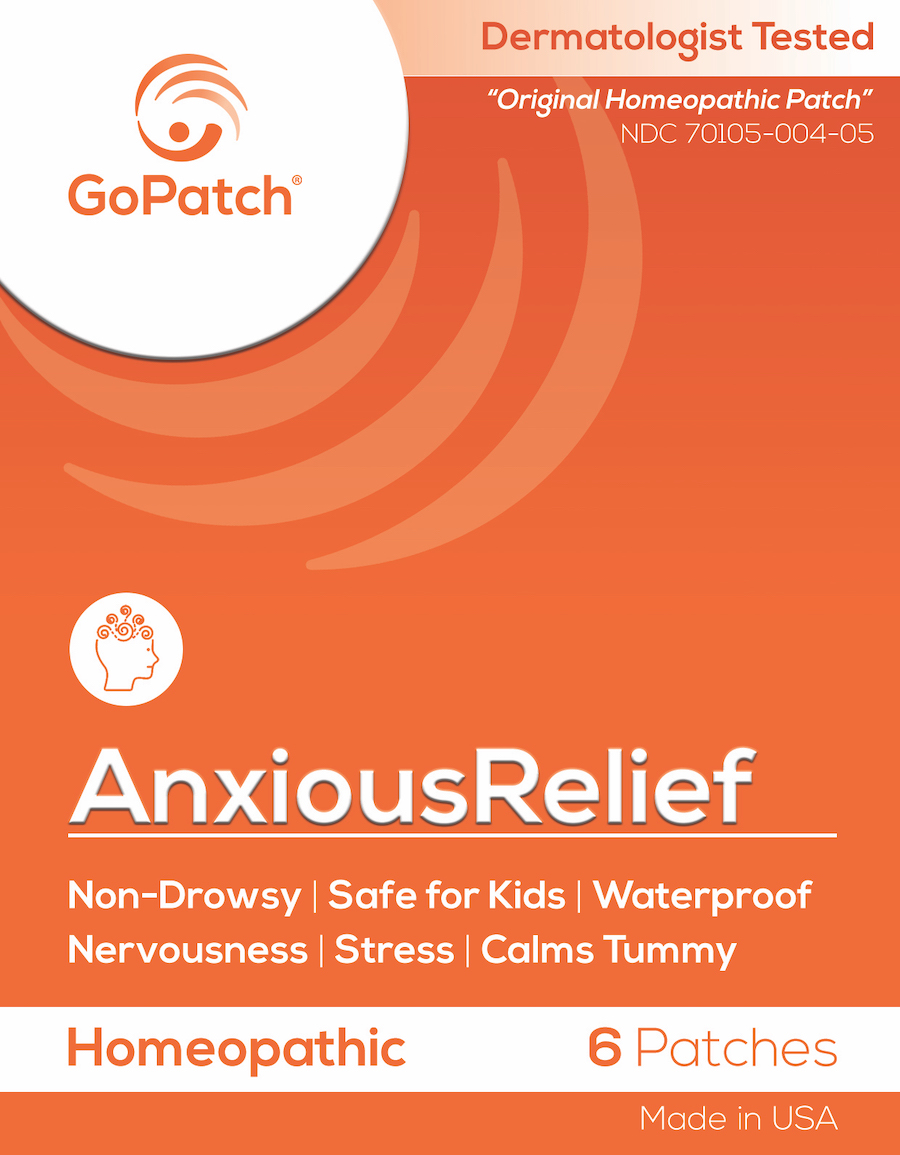 DRUG LABEL: AnxiousRelief
NDC: 70105-004 | Form: PATCH
Manufacturer: Centered Enterprises, LLC
Category: homeopathic | Type: HUMAN OTC DRUG LABEL
Date: 20240115

ACTIVE INGREDIENTS: CALENDULA OFFICINALIS FLOWERING TOP 3 [hp_X]/1 1; MATRICARIA RECUTITA 3 [hp_X]/1 1; SEPIA OFFICINALIS JUICE 3 [hp_C]/1 1; TOBACCO LEAF 6 [hp_C]/1 1; ANAMIRTA COCCULUS SEED 15 [hp_C]/1 1; STRYCHNOS NUX-VOMICA SEED 15 [hp_C]/1 1
INACTIVE INGREDIENTS: POLYVINYL ACETATE; WATER; ALCOHOL

AnxiousRelief Patch

Active ingredients | Purpose*
Cocculus Indicus 15C HPUS | anxiousness, nervousness, irritability
Nux Vomica 15C HPUS | irritability, upset stomach, sensitive to sound/light
Sepia 3C HPUS | restlessness, impatience, sadness
Tabacum 6C HPUS | sadness, nervous indigestion, frequent sighing
Chamomilla 3X HPUS | soothes skin
Calendula Officinalis 3X HPUS | irritability, upset stomach, sensitive to sound/light

The letters "HPUS" indicate that the components in this product are officially monographed in the Homeopathic Pharmacopoeia of the United States.

Purpose*
Cocculus Indicus - anxiousness, nervousness, irritability

Nux Vomica - irritability, upset stomach, sensitive to sound/light

Sepia - restlessness, impatience, sadness
Tabacum - sadness, nervous indigestion, frequent sighing
Chamomilla - soothes skin
Calendula Officinalis - irritability, upset stomach, sensitive to sound/light

The letters "HPUS" indicate that the components in this product are officially monographed in the Homeopathic Pharmacopoeia of the United States.

Uses

Temporarily relieves the symptoms of: ■ anxiousness ■ restlessness ■ nervousness ■ irritability ■ nervous stomach

Warnings

- For external use only.

Do Not Use

■ on wounds, broken, or irritated skin
■ if you have had reactions to adhesives

Stop Use

Stop use and ask a doctor if symptoms persist for more than 5 days or worsen.

If pregnant or breast-feeding, ask a health professional before use.

Ask Doctor

Ask doctor before use in children under 2 years of age.

- Keep out of the reach of children.

Directions

■ GoPatch must completely cover the navel.
■ Skin around navel must be clean, dry and free of lotions.
■ Remove GoPatch from sheet and apply completely covering navel.
■ Remove GoPatch no more than 12 hours after application.
■ Repeat as necessary.

Other information

- Store out of direct sunlight, in dry place, at 65-80°F (20-25°C).
- Contains no known allergens, free of latex, corn, soy, wheat, and yeast.
- If unsatisfied with GoPatch, please email us at WeCare@TheGoPatch.com for full money back guarantee.

Inactive ingredients Acrylic adhesive

Questions?

Questions or comments? Please call us at (707) 733-3011 or www.TheGoPatch.com

PACKAGE LABEL

GoPatch™

NDC 70105-001-05

Homeopathic